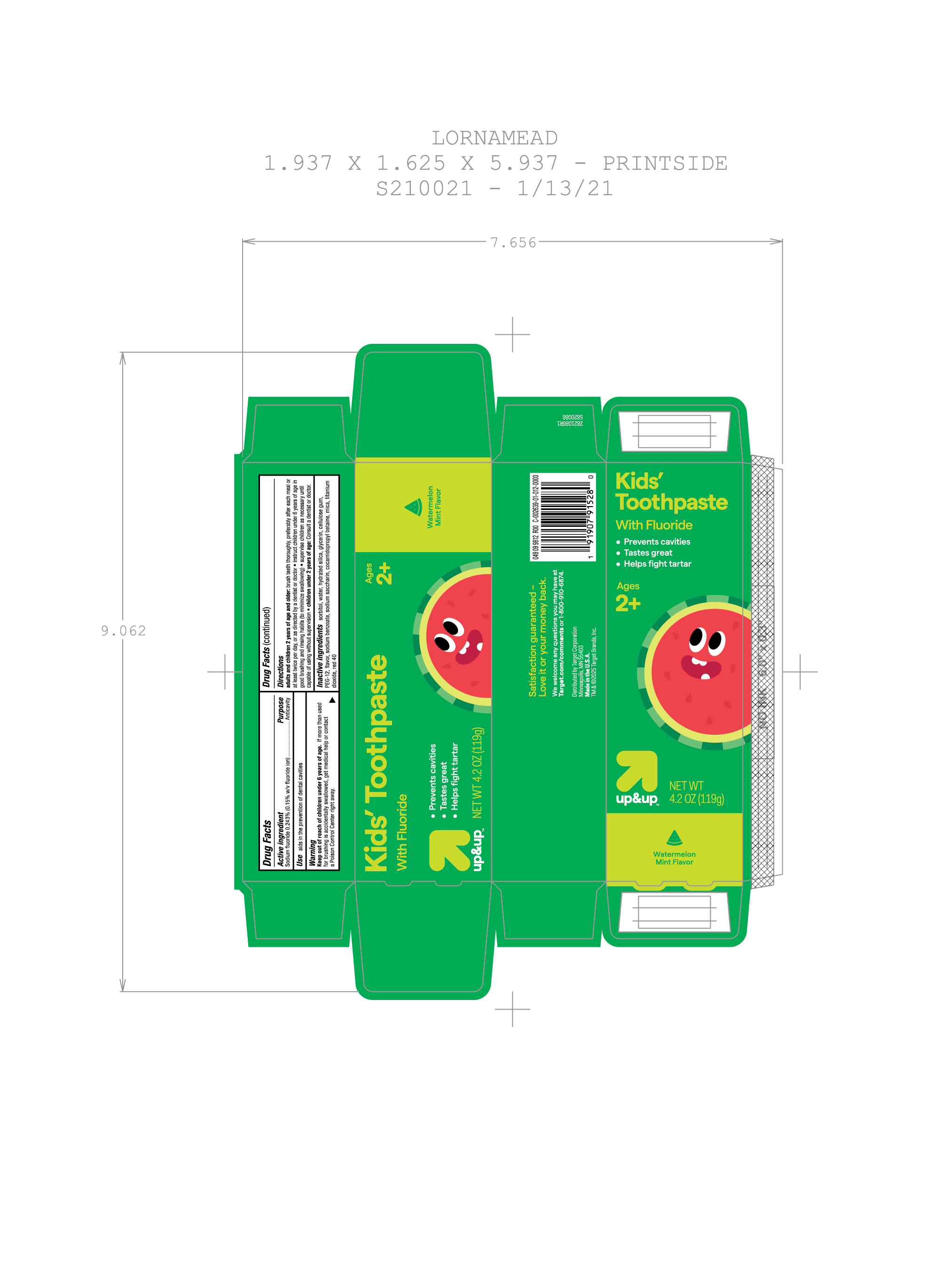 DRUG LABEL: Target
NDC: 11673-308 | Form: PASTE, DENTIFRICE
Manufacturer: Target
Category: otc | Type: HUMAN OTC DRUG LABEL
Date: 20251017

ACTIVE INGREDIENTS: SODIUM FLUORIDE 0.15 g/100 g
INACTIVE INGREDIENTS: SODIUM SACCHARIN; SORBITOL; PEG-12; FD&C RED NO. 40; GLYCERIN; CELLULOSE GUM; COCAMIDOPROPYL BETAINE; WATER; SODIUM BENZOATE; TITANIUM DIOXIDE; HYDRATED SILICA; MICA

5820086 Target Up&Up Kids Watermelon Mint (80-15188)

ACTIVE INGREDIENT

Sodium fluoride 0.243% (0.15% w/v fluoride ion) ......... Anticavity

PURPOSE

Anticavity

INDICATIONS AND USAGE

aids in the preventnion of dental cavities

Keep out of reach of children 6 years of age.

Keep out of reach of children under 6 years of age. If more than used for brushing is accidentally swallowed, get medical help or contact a Posion Control right away.

DOSAGE AND ADMINISTRATION

adults and children 2 years of age and older: brush teeth thoroughly, preferably after each meal or at least twice per day, or as directed by a dentist or doctor

- instruct children under 6 years of age in good brushing and rinsing habits (to minimize swallowing)
- supersive children as necessary until capable of using without supervision
- children under 2 years of age: Consult a dentist or doctor

INACTIVE INGREDIENT

sorbitol, water, hydrated silica, glycerin, cellulose gum, PEG-12, flavor, sodium benzoate, sodium saccharin, cocamidopropyl betaine, mica, titanium dioxide, red 40